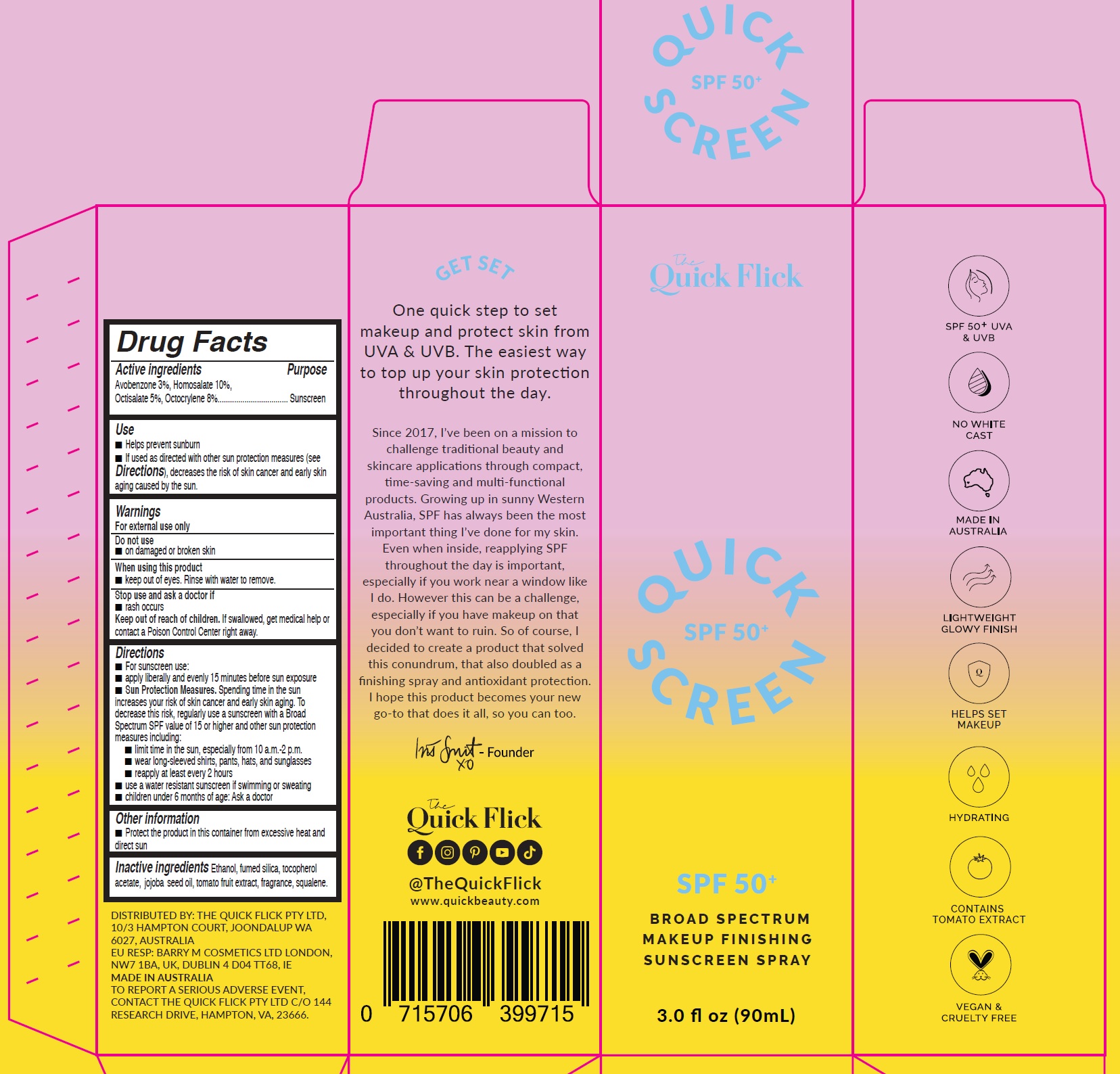 DRUG LABEL: Quick Screen Sunscreen SPF 50
NDC: 82654-000 | Form: LOTION
Manufacturer: The Quick Flick PTY LTD
Category: otc | Type: HUMAN OTC DRUG LABEL
Date: 20250212

ACTIVE INGREDIENTS: AVOBENZONE 30 mg/1 mL; HOMOSALATE 100 mg/1 mL; OCTISALATE 50 mg/1 mL; OCTOCRYLENE 80 mg/1 mL
INACTIVE INGREDIENTS: ALCOHOL; .ALPHA.-TOCOPHEROL ACETATE; JOJOBA OIL; SQUALENE

Quick Screen Sunscreen Spray SPF 50+

Active ingredients

Avobenzone 3%, Homosalate 10%, Octisalate 5%, Octocrylene 8%

Purpose

Sunscreen

Use

- Helps prevent sunburn
- If used as directed with other sun protection measures (see Directions), decreases the risk of skin cancer and early skinaging caused by the sun.

Warnings

For external use only

Do not use

- on damaged or broken skin

When using this product

- keep out of eyes. Rinse with water to remove.

Stop use and ask a doctor if

- rash occurs

Keep out of reach of children.

If swallowed, get medical help or contact a Poison Control Center right away.

Directions

- For sunscreen use:
- apply liberally and evenly 15 minutes before sun exposure
- Spending time in the sun increases your risk of skin cancer and early skin aging. To decrease this risk, regularly use a sunscreen with a Broad Spectrum SPF value of 15 or higher and other sun protection measures including: Sun Protection Measures.
- limit time in the sun, especially from 10 a.m.-2 p.m.
- wear long-sleeved shirts, pants, hats, and sunglasses
- reapply at least every 2 hours
- use a water resistant sunscreen if swimming or sweating
- children under 6 months of age: Ask a doctor

Other information

- Protect the product in this container from excessive heat and direct sun

Inactive ingredients

Ethanol, fumed silica, tocopherol acetate, jojoba seed oil, tomato fruit extract, fragrance, squalene.